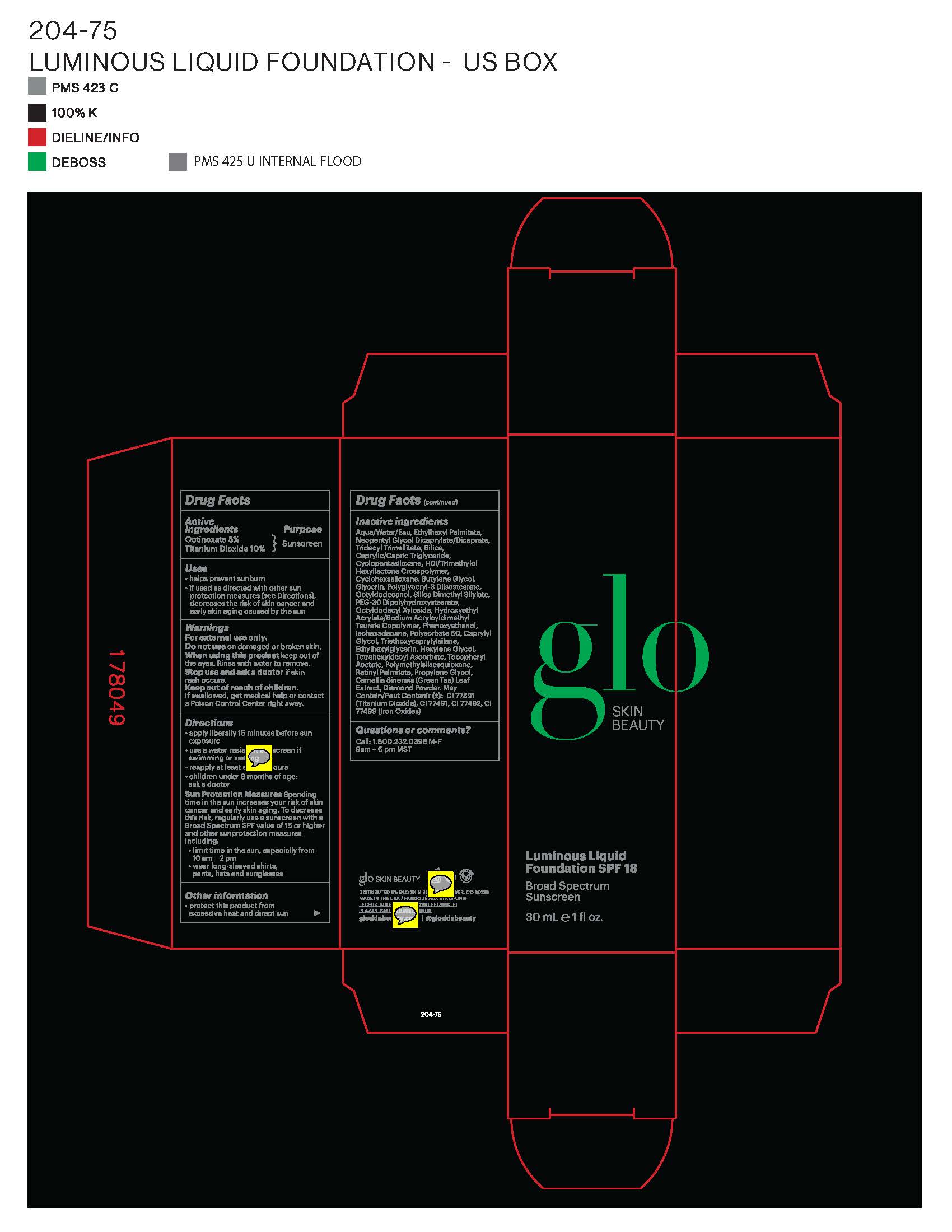 DRUG LABEL: glo SKIN BEAUTY Luminous Liquid Foundation SPF 18
NDC: 60541-1310 | Form: CREAM
Manufacturer: Hayden Caleel LLC
Category: otc | Type: HUMAN OTC DRUG LABEL
Date: 20250105

ACTIVE INGREDIENTS: TITANIUM DIOXIDE 10 g/100 g; OCTINOXATE 5 g/100 g
INACTIVE INGREDIENTS: ETHYL PALMITATE; NEOPENTYL GLYCOL DICAPRYLATE/DICAPRATE; TRIDECYL TRIMELLITATE; SILICON; CAPRYLIC/CAPRIC/LAURIC TRIGLYCERIDE; BUTYLENE GLYCOL; GLYCERIN; POLYGLYCERYL-3 DIISOSTEARATE; OCTYLDODECANOL; PEG-30 DIPOLYHYDROXYSTEARATE; SILICA DIMETHYL SILYLATE; PHENOXYETHANOL; HYDROXYETHYL ACRYLATE/SODIUM ACRYLOYLDIMETHYL TAURATE COPOLYMER (100000 MPA.S AT 1.5%); ISOHEXADECANE; POLYSORBATE 60; CAPRYLYL GLYCOL; ETHYLHEXYLGLYCERIN; TETRAHEXYLDECYL ASCORBATE; WATER; ALPHA-TOCOPHEROL; POLYMETHYLSILSESQUIOXANE (11 MICRONS); DIMETHICONE; TRIETHOXYCAPRYLYLSILANE; HEXYLENE GLYCOL; CAMELLIA OLEIFERA LEAF

DRUG FACTS

Active Ingredients

Octinoxate 5%

Titanium Dioxide 6.5%

Uses

• helps prevent sunburn • if used as directed with other
sun protection measures (see Directions), decreases the
risk of skin cancer and early skin aging caused by the sun

Warnings

For external use only
Do not use on damaged or broken skin
When using this product keep out of eyes. Rinse with water to remove.
Stop use and ask a docor if rash occurs
Keep out of reach of children. If swalled, get medical help or contact a Poison Control Center right away.

Directions

• apply generously 15 minutes before sun exposure
• reapply at least every 2 hours
• use a water-resistant sunscreen if swimming or sweating
• Sun Protection Measures. Spending time in the sun
increases your risk of skin cancer and early skin aging. To decrease
this risk, regularly use a sunscreen with a Broad Spectrum SPF
value of 15 or higher and other sun protection measures including:
• limit time in the sun, especially from 10 a.m. - 2 p.m.
• wear long-sleeved shirts, pants, hats, and sunglasses
• children under 6 months of age: Ask a doctor

Inactive ingredients

Aqua/Water/Eau, Ethyl Palmitate, Neopentyl Glycol Dicaprylate/Dicaprate, Tridecyl Trimellitate, Silica, Cyclopentasiloxane, Caprylic/Capric Trigylceride, HDI/Trimethylol Hexyllactone Crosspolymer, Butylene Glycol, Glycerin, Polyglyceryl-3 Diisostearate, Cyclohexasiloxane, Octyldodecanol, Octyldodecyl Xyloside, PEG-30 Dipolyhydroxystearate, Silica Dimethyl Siylate, Phenoxyethanol, Hydroxyethylacrylate/Sodium Acryloyldimethyl Tuarate Copolymer, Isohexadecane, Polysorbate 60, Caprylyl Glycol, Ethylhexyl Glycerin, Tetrahexyldecyl Ascorbate, Tocopheryl Acetate, Polymethylsilsesquioxane, Dimethicone, Retinyl Palmitate, Triethoxycaprylylsilane, Hexylene Gylcol, Camellia Oleifera Leaf Extract, Diamond Powder, Titanium Dioxide, Iron Oxides

Other Information

• protect the product in this container from excessive
heat and direct sun

Keep out of reach of children

Purpose

Sunscreen